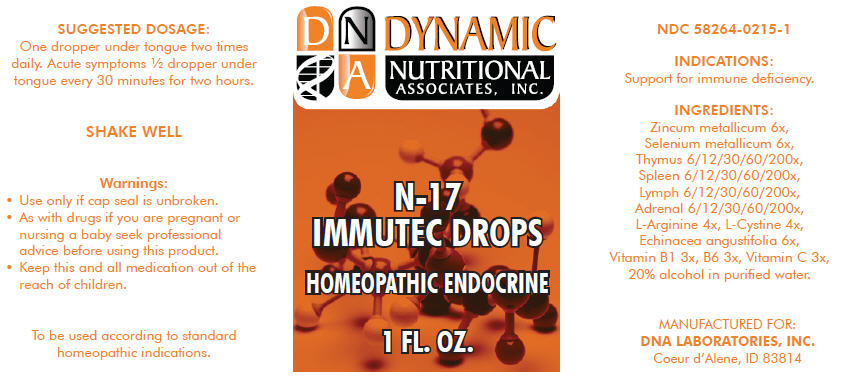 DRUG LABEL: N-17
NDC: 58264-0215 | Form: SOLUTION
Manufacturer: DNA Labs, Inc.
Category: homeopathic | Type: HUMAN OTC DRUG LABEL
Date: 20250109

ACTIVE INGREDIENTS: ZINC 6 [hp_X]/1 mL; SELENIUM 6 [hp_X]/1 mL; BOS TAURUS THYMUS 200 [hp_X]/1 mL; SUS SCROFA SPLEEN 200 [hp_X]/1 mL; BOS TAURUS LYMPH 200 [hp_X]/1 mL; BOS TAURUS ADRENAL GLAND 200 [hp_X]/1 mL; ARGININE 4 [hp_X]/1 mL; CYSTINE 4 [hp_X]/1 mL; ECHINACEA ANGUSTIFOLIA 6 [hp_X]/1 mL; THIAMINE 3 [hp_X]/1 mL; PYRIDOXINE HYDROCHLORIDE 3 [hp_X]/1 mL; ASCORBIC ACID 3 [hp_X]/1 mL
INACTIVE INGREDIENTS: ALCOHOL; WATER

N-17

NDC 58264-0215-1

INDICATIONS

PURPOSE

Support for immune deficiency.

ACTIVE INGREDIENT

INGREDIENTS

Zincum metallicum 6x, Selenium metallicum 6x, Thymus 6/12/30/60/200x, Spleen 6/12/30/60/200x, Lymph 6/12/30/60/200x, Adrenal 6/12/30/60/200x, L-Arginine 4x, L-Cystine 4x, Echinacea angustifolia 6x, Vitamin B1 3x, B6 3x, Vitamin C 3x, 20% alcohol in purified water.

SUGGESTED DOSAGE

One dropper under tongue two times daily. Acute symptoms ½ dropper under tongue every 30 minutes for two hours.

STORAGE AND HANDLING

SHAKE WELL

Warnings

- Use only if cap seal is unbroken.

PREGNANCY OR BREAST FEEDING

- As with drugs if you are pregnant or nursing a baby seek professional advice before using this product.

KEEP OUT OF REACH OF CHILDREN

- Keep this and all medication out of the reach of children.

To be used according to standard homeopathic indications.

PRINCIPAL DISPLAY PANEL - 1 FL. OZ. Bottle Label

DYNAMIC
NUTRITIONAL
ASSOCIATES, INC.

N-17

IMMUTEC DROPS

HOMEOPATHIC ENDOCRINE

1 FL. OZ.